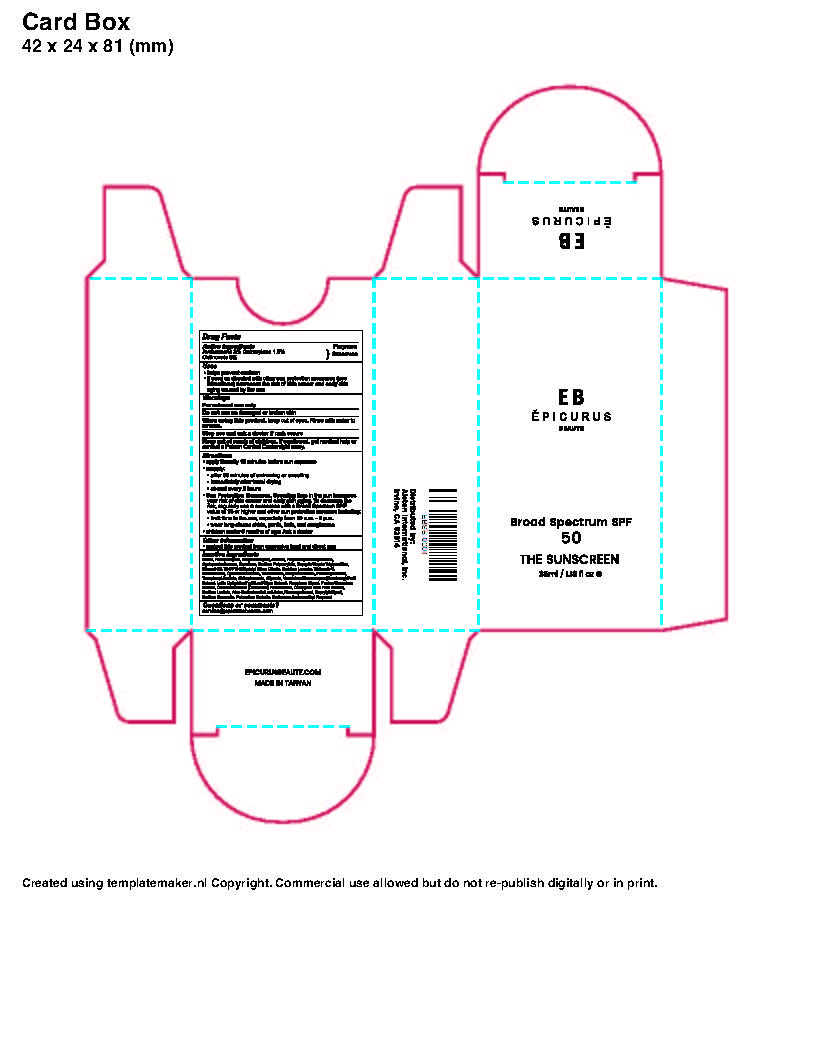 DRUG LABEL: EB Epicurus  SPF 50 The Sunscreen
NDC: 81901-001 | Form: LOTION
Manufacturer: BIOCROWN BIOTECHNOLOGY CO., LTD
Category: otc | Type: HUMAN OTC DRUG LABEL
Date: 20210602

ACTIVE INGREDIENTS: OCTINOXATE 30 mg/1 mL; OCTOCRYLENE 15 mg/1 mL; AVOBENZONE 30 mg/1 mL
INACTIVE INGREDIENTS: BUTYLENE GLYCOL; ALCOHOL; POLYMETHYLSILSESQUIOXANE (4.5 MICRONS); MINERAL OIL; SODIUM BENZOATE; AMINOMETHYLPROPANOL; POLYACRYLIC ACID (8000 MW); 2,4,6,8-TETRAMETHYLTETRAPHENYLCYCLOTETRASILOXANE, (2.ALPHA.,4.ALPHA.,6.BETA.,8.BETA.)-; PHOSPHATIDYLCHOLINE, SOYBEAN; PPG-3 MYRISTYL ETHER; CYCLOMETHICONE 4; WATER; SQUALANE; PPG-1 TRIDECETH-6; DIMETHICONE; TRIISOSTEARIN; DECYL GLUCOSIDE; CHLORPHENESIN; SODIUM LACTATE; POTASSIUM SORBATE; GLYCERIN; DIOSPYROS KAKI LEAF; CAPRYLYL GLYCOL; SORBITAN MONOLAURATE; CRANBERRY JUICE; .ALPHA.-TOCOPHEROL ACETATE, D-; CUCUMBER; ALOE VERA LEAF; PHENOXYETHANOL; SODIUM ACRYLATE; MEDIUM-CHAIN TRIGLYCERIDES

EB Epicurus SPF 50 The Sunscreen

Active ingredients

Avobenzone 3%

Octocrylene 1.5%

Octinoxate 3%

Purpose

Sunscreen

Uses

• helps prevent sunburn • if used as directed with other sun protection measures (see Directions) decreases the risk of skin cancer and early skin aging caused by the sun.

Warnings

For external use only

Do not use

- on damaged or broken skin

When using this product

- keep out of eyes. Rinse with water to remove

Stop use and ask a doctor

- if rash occurs

Keep out of reach of children

- If this product is swallowed get medical help or contact a Poison Control Centre right away.

Directions

Apply liberally 15 minutes before sun exposure
Reapply:

- after 80 minutes of swimming or sweating
- immediately after towel drying
- at least every 2 hours

Sun Protection Measures

- Spending time in the sun increases your risk of skin cancer and early skin aging. To decrease the risk, regularly use a sunscreen with a Broad Spectrun SPF value of 15 of higher and other sun protection measure including:
- limit time in the sun, especially from 10am-2pm
- wear long-sleeve shirts, pants, hats and sunglasses
- children under 6 months of age: Ask a doctor

Other information

• Protect this product from excessive heat and direct sun

Inactive ingredients

Water, Phospholipids, Butylene Glycol, Alcohol, Polymethylsilsesquioxane, Cyclopentasiloxane, Squalane, Sodium Polyacrylate, Caprylic/Capric Triglycerides, Mineral Oil, Tri-PPG-3 Myristyl Ether Citrate, Sorbitan Laurate, Trideceth-6, Dimethicone, Cyclotetrasiloxane, Triisostearin, Decyl Glucoside, tocopheryl acetate, Chlorphenesin, Glycerin, Vaccinium Macrocarpon (Cranberry) Fruit Extract, Cucumis Sativus (Cucumber) Fruit Extract, Diospyros Kaki Fruit Extract, Sodium Lactate, Aloe Barbadensis Leaf Juice, Phenoxyethanol, Caprylyl Glycol, Sodium Benzoate, Potassium Sorbate, Carbomer, aminomethyl propanol.

Questions?

service@epicurusbeaute.com